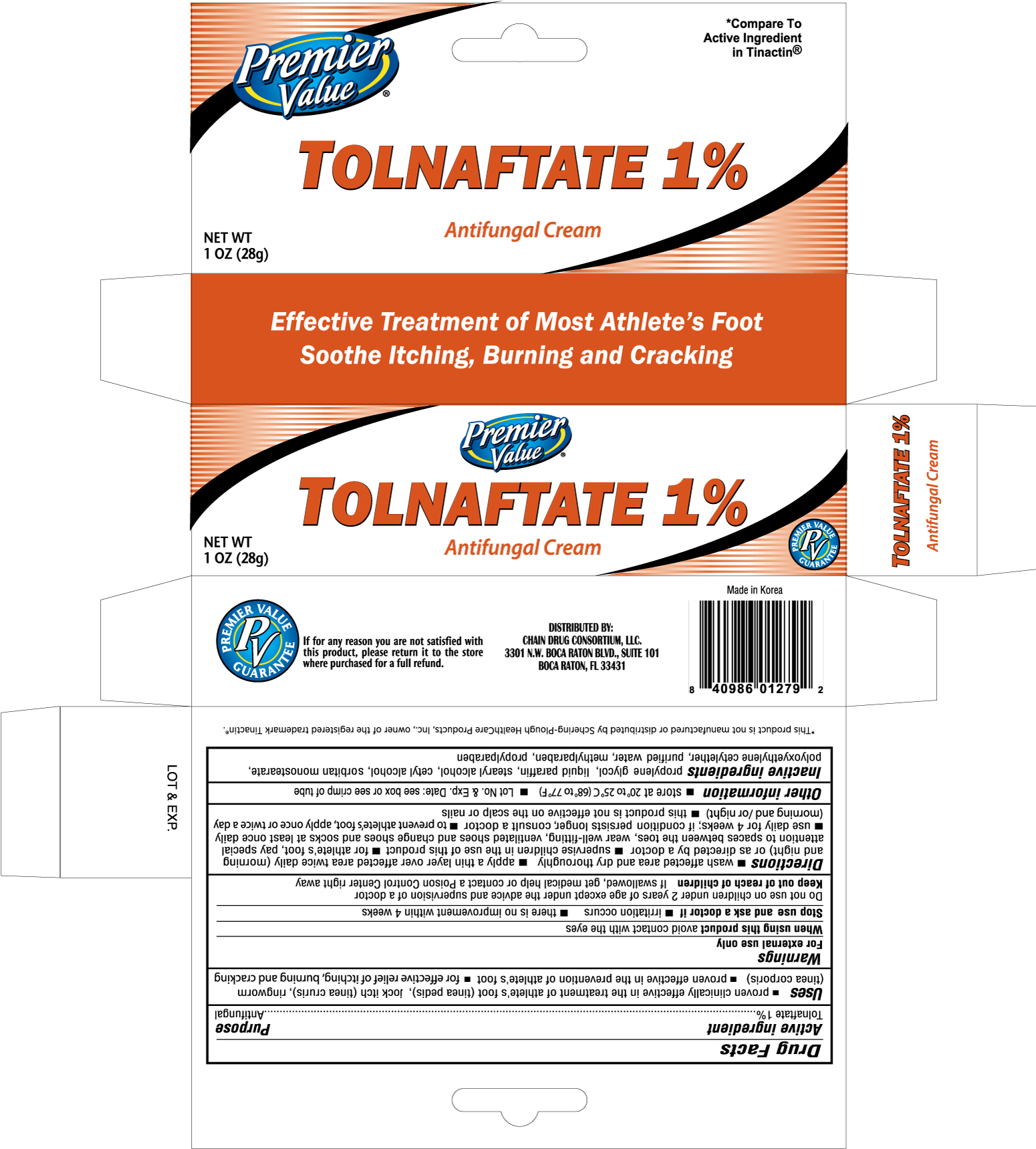 DRUG LABEL: PREMIER VALUE TOLNAFTATE ANTIFUNGAL
NDC: 68016-014 | Form: CREAM
Manufacturer: CHAIN DRUG CONSORTIUM, LLC
Category: otc | Type: HUMAN OTC DRUG LABEL
Date: 20120120

ACTIVE INGREDIENTS: TOLNAFTATE 10 mg/1 g
INACTIVE INGREDIENTS: PROPYLENE GLYCOL; MINERAL OIL; STEARYL ALCOHOL; CETYL ALCOHOL; SORBITAN MONOSTEARATE; WATER; METHYLPARABEN; PROPYLPARABEN

Drug Facts

Active Ingredient Purpose

Tolnaftate 1% .................................................................................Antifungal

Uses

- proven clinically effective in the treatment of athlete's foot (tinea pedis), jock itch (tinea cruris), ringworm (tinea corporis)
- proven effective in the prevention of athlete's foot
- effectively soothes and relieves itching associated with jock itch, scaly skin between the toes and burning feet

Warnings

For external use only

When using this product avoid contact with the eyes.

Stop use and ask a doctor if

- irritation occurs
- there is no improvement within 4 weeks

Do not use on children under 2 years of age except under the advice and supervision of a doctor.

Keep out of reach of children. If swallowed, get medical help or contact a Poison Control Center right away.

Directions

- Wash affected area and dry thoroughly
- Apply a thin layer over affected area twice daily (morning and night) or as directed by a doctor
- Supervise children in the use of this product
- For athlete's foot, pay special attention to spaces between the toes, wear well-fitting, ventilated shoes and change shoes and socks at least once daily
- For athlete's foot and ringworm use daily for 4 weeks, for jock itch use daily for 2 weeks. If condition persists longer consult a doctor
- This product is not effective on the scalp or nails

Other Information

Lot No. and Exp. Date: see box or see crimp of the tube. Store between 20o to 25oC (68o to 77oF)

Inactive Ingredients

Propylene glycol, liquid paraffin, stearyl alchol, cetyl alcohol, sorbitan monstearate, polyoxyethylene cetylether, purified water, methylparaben, propylparaben.

DOSAGE AND ADMINISTRATION

DISTRIBUTED BY:

CHAIN DRUG CONSORTIUM, LLC.

3301 N.W. BOCA RATON BLVD., SUITE 101

BOCA RATON, FL 33431

MADE IN KOREA

PACKAGE LABEL

Enter section text here